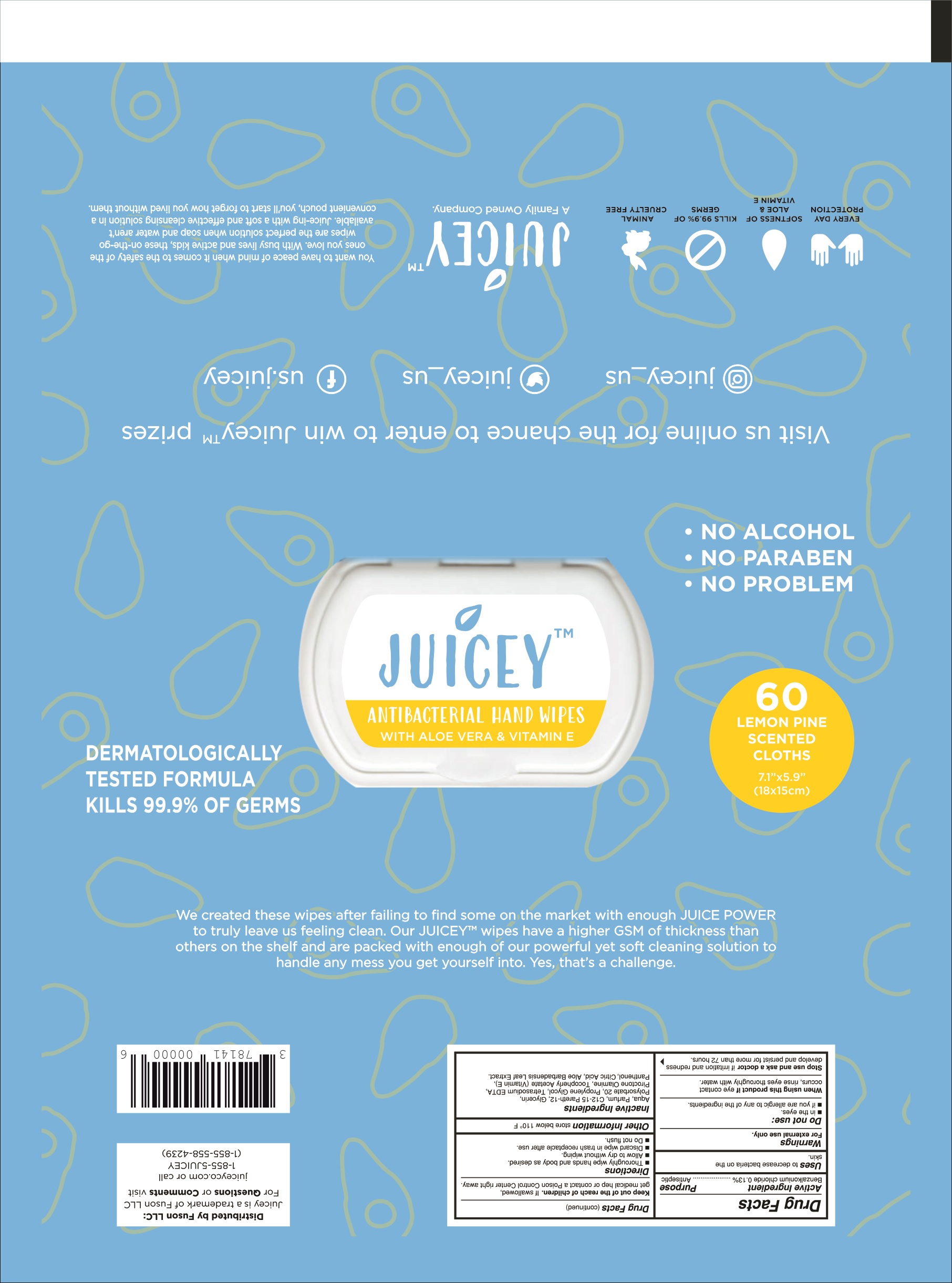 DRUG LABEL: Juicey Antibacterial Hand Wipes
NDC: 76964-901 | Form: CLOTH
Manufacturer: TAT KIMYA SABUN VE GLISERIN SANAYI VE TICARET ANONIM SIRKETI
Category: otc | Type: HUMAN OTC DRUG LABEL
Date: 20201028

ACTIVE INGREDIENTS: BENZALKONIUM CHLORIDE 0.13 g/100 g
INACTIVE INGREDIENTS: ALOE VERA LEAF 0.001 g/100 g; C12-15 PARETH-12 0.35 g/100 g; PROPYLENE GLYCOL 0.2 g/100 g; POLYSORBATE 20 0.2 g/100 g; PIROCTONE OLAMINE 0.1 g/100 g; GLYCERIN 0.25 g/100 g; EDETATE SODIUM 0.1 g/100 g; PANTHENOL 0.001 g/100 g; .ALPHA.-TOCOPHEROL ACETATE 0.001 g/100 g; WATER 98.66 g/100 g; CITRIC ACID MONOHYDRATE 0.008 g/100 g

Active Ingredient(s)

Benzalkonium Chloride %0.25 w/w. Purpose : Antibacterial

Purpose

Antibacterial, Wet Wipes

Use

Antibacterial wet wipes helps reduce bacteria (organisms).

Effective on bacterias :

Staphylococcus aureus ATCC 6538,

Pseudomonas aeruginosa ATCC 15442,

Enterococcus hirae ATCC 10541,

Escherichia coli ATCC 10536

Warnings

Keep away from children and direct sunlight. Children should not use this product without an adult supervision. For external use only. In case of poisoning, call the National Toxitation Information Center. Awoid contact with eyes.

Do not use with eyes. For external use only.

WHEN USING

In case of inhaling: If you feel uncomfortable get some fresh ait. In case of skin Irritation: Occurs stop using the wipes immediately and wash the affected area with water and soap for at least 15 minutes. People with sensitive skin, pregnant women, breastfeeding women and children under the age of 12 should consult a doctor/pharmacist before using the product. Seek for medical advice if necessary. In case of contact with eyes: If you are wearing contact lenses, remove them immediately. Rince your eyes with plenty of clean water. In case of swallowing: Call your local Toxication Center and get medical help. There is no specific antidote therefore treatment must be done according to symptoms. Treatment: Treatment is indicated according to the indication. CALL YOUR LOCAL POISON CENTER.

STOP USE

Treatment is indicated according to the indication. CALL YOUR LOCAL POISON CENTER

Keep out of reach of children. Children should not use this product without an adult supervision.

Directions

Provides practical cleaning without need of water and soap. Used for hand cleaning. Open the adhesive label and pick up a wipe. Gently wipe your hands with antibacterial wipe. No rinsing required. User group : General public

Other Information

Store in a cool and dry place.

Inactive Ingredients

Aqua, Parfum, C12-15 Pareth-12, Glycerin, Polysorbate 20, Propylene Glycol, Tetrasodium EDTA, Piroctone Olamine, Tocopheryl Acetate, Panthenol, Citric Acid, Aloe Barbadensis Leaf Extract